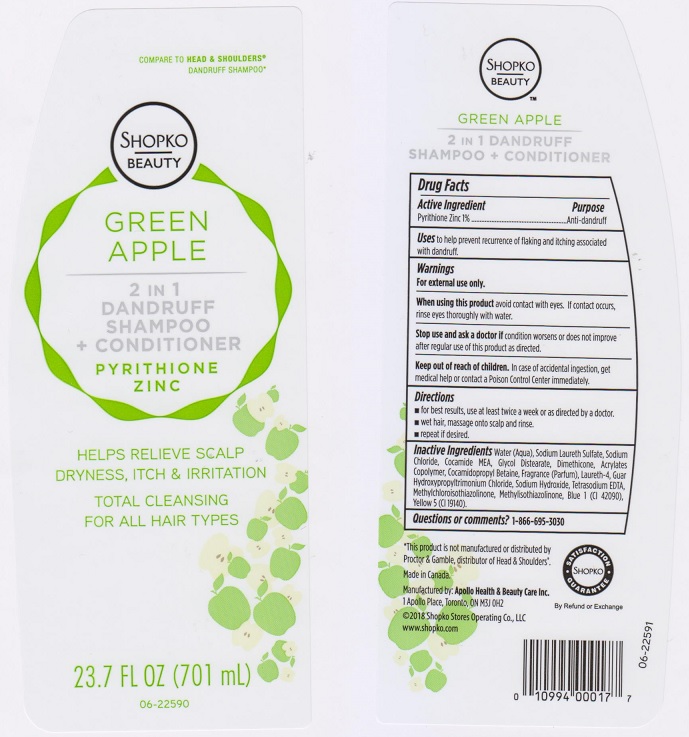 DRUG LABEL: Shopko Beauty Green Apple 2 in 1 Dandruff
NDC: 63148-002 | Form: SHAMPOO
Manufacturer: Apollo Health and Beauty Care Inc.
Category: otc | Type: HUMAN OTC DRUG LABEL
Date: 20180216

ACTIVE INGREDIENTS: PYRITHIONE ZINC 10 mg/1 mL
INACTIVE INGREDIENTS: WATER; SODIUM LAURETH SULFATE; SODIUM CHLORIDE; COCO MONOETHANOLAMIDE; GLYCOL DISTEARATE; METHACRYLIC ACID - METHYL METHACRYLATE COPOLYMER (1:1); COCAMIDOPROPYL BETAINE; LAURETH-4; GUAR HYDROXYPROPYLTRIMONIUM CHLORIDE (1.7 SUBSTITUENTS PER SACCHARIDE); SODIUM HYDROXIDE; EDETATE SODIUM; METHYLCHLOROISOTHIAZOLINONE; METHYLISOTHIAZOLINONE; FD&C BLUE NO. 1; FD&C YELLOW NO. 5

Drug Facts

Active ingredient

Pyrithione Zinc 1%

Purpose

Anti-dandruff

Uses

to help prevent recurrence of flaking and itching associated with dandruff.

Warnings

For external use only.

When using this product

avoid contact with eyes. If contact occurs, rinse eyes thoroughly with water.

Stop use and ask a doctor if

condition worsens or does not improve after regular use of this product as directed.

Keep out of reach of children.

In case of accidental ingestion, get medical help or contact a Poison Control Center immediately.

Directions

- for best results, use at least twice a week or as directed by a doctor.
- wet hair, massage onto scalp and rinse.
- repeat if desired.

Inactive ingredients

Water (Aqua), Sodium Laureth Sulfate, Cocamide MEA, Glycol Distearate, Dimethicone, Acrylates Copolymer, Cocamidopropyl Betaine, Fragrance (Parfum), Laureth-4, Guar Hydroxypropyltrimonium Chloride, Sodium Hydroxide, Tetrasodium EDTA, Methylchloroisothiazolinone, Methylisothiazolinone, Blue 1 (CI 42090), Yellow 5 (CI 19140).

Questions or comments?

1-866-695-3030